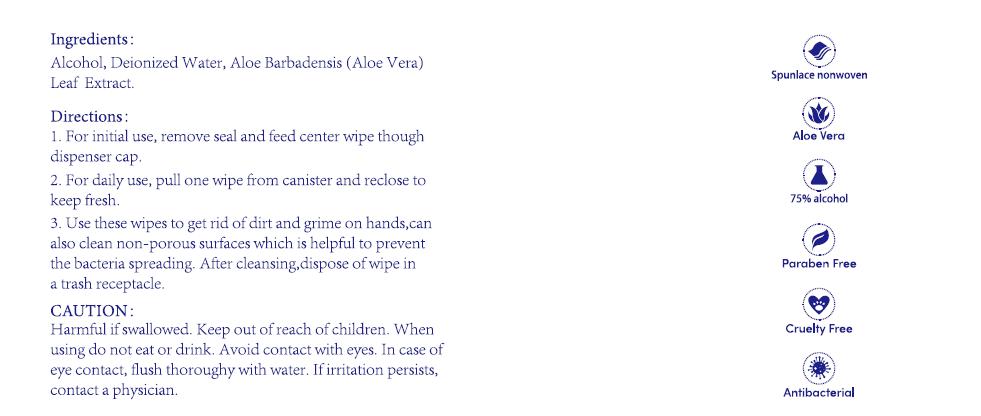 DRUG LABEL: Alcohol Wipes
NDC: 78936-016 | Form: CLOTH
Manufacturer: Hangzhou Caring Cleaning Commodity Co.,Ltd
Category: otc | Type: HUMAN OTC DRUG LABEL
Date: 20200819

ACTIVE INGREDIENTS: ALCOHOL 75 g/100 g
INACTIVE INGREDIENTS: ALOE VERA LEAF; WATER

Alcohol Wipes

Active Ingredient(s)

Alcohol 75%

Purpose

Antiseptic

Use

Decreases bacteria on hands

Warnings

Harmful if swallowed.

If irritation persists, contact a physician.

When using this product

When using do not eat or drink.

Avoid contact with eyes; in case of eye contact, flush thoroughly with water

Keep out of reach of children

Directions

1. For initial use, remove seal and feed center wipe though dispenser cap.

2. For daily use, pull one wipe from canister and reclose to keep fresh.

3. Use these wipes to get rid of dirt and grime on hands, can also clean non-porous surfaces which is helpful to prevent the bacteria spreading. After cleansing, dispose of wipe in a trash receptacle.

Inactive ingredients

Deionized Water, Aloe Barbadensis(Aloe Vera) Leaf Extract.

Package Label - Principal Display Panel

70 POUCH IN 1 CANISTER NDC: 78936-016-01